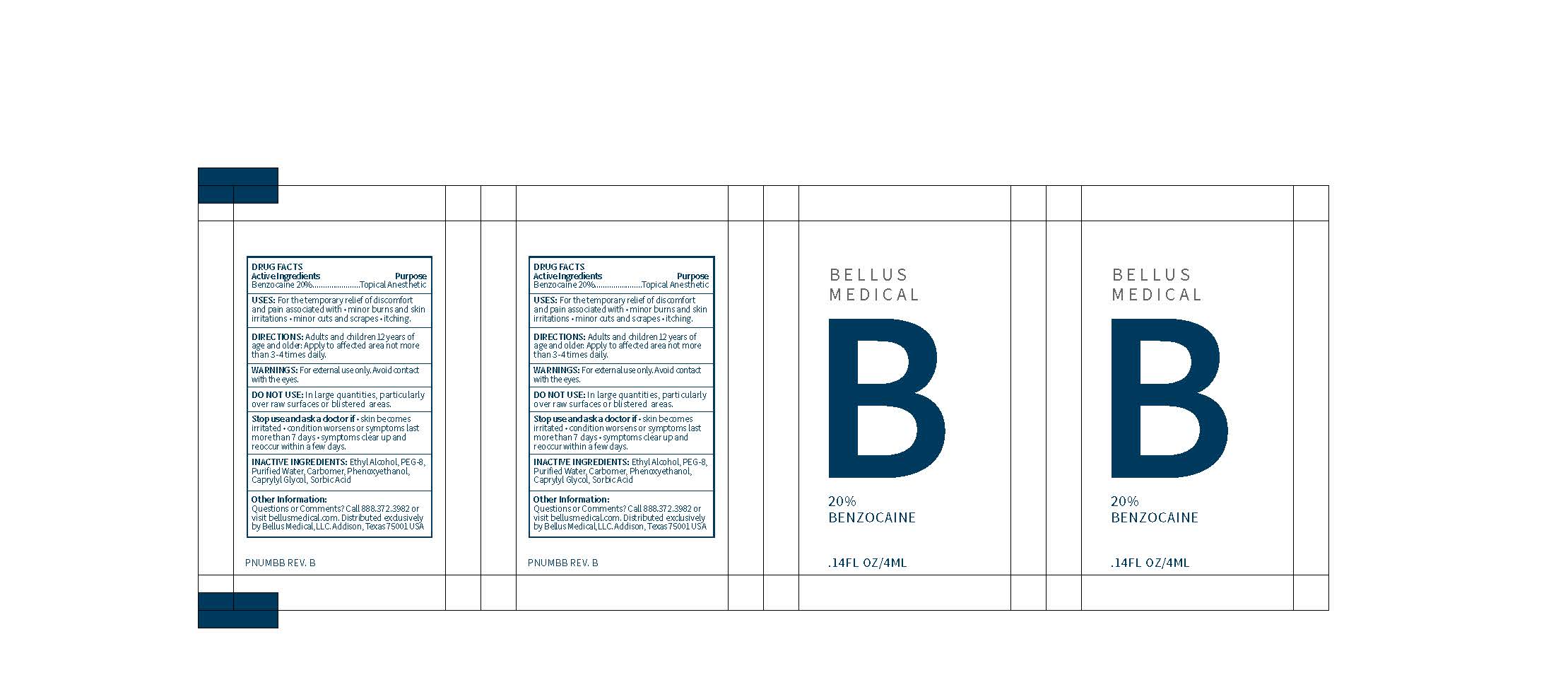 DRUG LABEL: Benzocaine
NDC: 71888-101 | Form: GEL
Manufacturer: Bellus Medical, LLC
Category: otc | Type: HUMAN OTC DRUG LABEL
Date: 20241118

ACTIVE INGREDIENTS: BENZOCAINE 200 mg/1 mL
INACTIVE INGREDIENTS: POLYETHYLENE GLYCOL 400; SORBIC ACID; PHENOXYETHANOL; CAPRYLYL GLYCOL; ALCOHOL; WATER; CARBOXYPOLYMETHYLENE

20% Benzocaine Gel

ACTIVE INGREDIENT

Benzocaine 20%

INACTIVE INGREDIENT

EthylAlcohol, PEG-8, Purified Water, Carbomer, Phenoxyethanol, Caprylyl Glycol, Sorbic Acid

DOSAGE AND ADMINISTRATION

USES: For the temporary relief of discomfort and pain associated with

- minor burns and skin irritations
- minor cuts and scrapes
- itching

DIRECTIONS: Adults and children 12 years of age and older: Apply to affected area not more than 3-4 times daily.

WARNINGS

For external use only. Avoid contact with the eyes.

Stop use and ask a doctor if:

- Skin becomes irritated
- Condition worsens or symptoms last more than 7 days
- Symptoms clear up and reoccur within a few days

DO NOT USE: in large quantities, particularly over raw surfaces or blistered areas.

PURPOSE

Topical Anesthetic

INDICATIONS AND USAGE

USES: For the temporary relief of discomfort and pain associated with

- minor burns and skin irritations
- minor cuts and scrapes
- itching

DIRECTIONS: Adults and children 12 years of age and older: Apply to affected area not more than 3-4 times daily.

Keep out of reach of children.